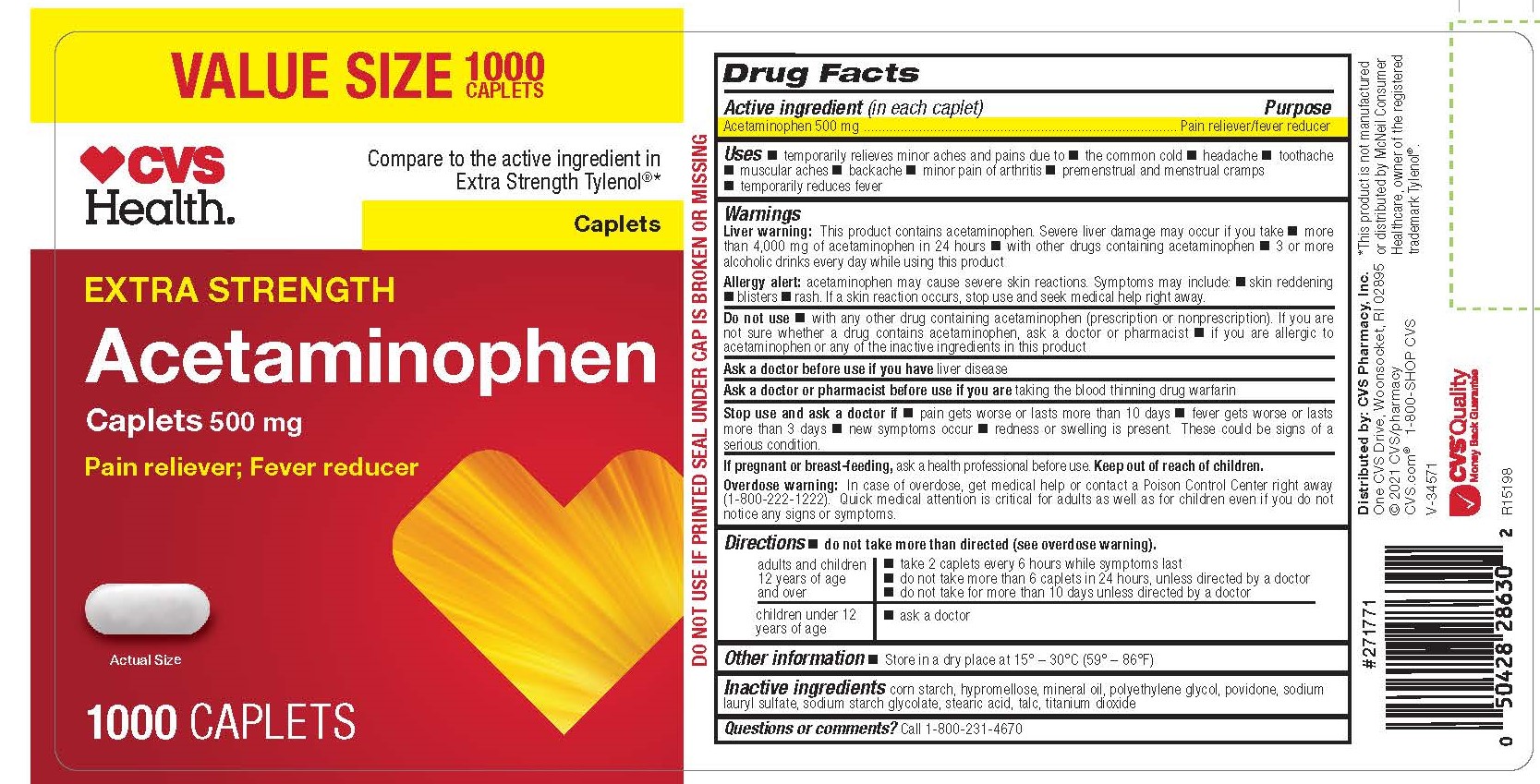 DRUG LABEL: Acetaminophen
NDC: 69842-864 | Form: TABLET, FILM COATED
Manufacturer: CVS Pharmacy, Inc
Category: otc | Type: HUMAN OTC DRUG LABEL
Date: 20241202

ACTIVE INGREDIENTS: ACETAMINOPHEN 500 mg/1 1
INACTIVE INGREDIENTS: STEARIC ACID; LIGHT MINERAL OIL; SODIUM STARCH GLYCOLATE TYPE A POTATO; HYPROMELLOSES; POLYETHYLENE GLYCOL 400; POVIDONE K30; TITANIUM DIOXIDE; TALC; SODIUM LAURYL SULFATE; STARCH, CORN

1190-CVS

Drug Facts

Active ingredient (in each caplet)
Acetaminophen 500 mg

Purpose
Pain reliever/fever reducer

Uses

 temporarily relieves minor aches and pains due to  the common cold  headache  toothache
 muscular aches

 backache

 minor pain of arthritis

 premenstrual and menstrual cramps
 temporarily reduces fever

WARNINGS

Liver warning: This product contains acetaminophen. Severe liver damage may occur if you take

 more than 4,000 mg of acetaminophen in 24 hours

 with other drugs containing acetaminophen

 3 or more alcoholic drinks every day while using this product
Allergy alert: acetaminophen may cause severe skin reactions. Symptoms may include:  skin reddening  blisters  rash. If a skin reaction occurs, stop use and seek medical help right away.

DO NOT USE

 with any other drug containing acetaminophen (prescription or nonprescription). If you are not sure whether a drug contains acetaminophen, ask a doctor or pharmacist

 if you are allergic to acetaminophen or any of the inactive ingredients in this product

Ask a doctor before use if you have liver disease

Ask a doctor or pharmacist before use if you are taking the blood thinning drug warfarin

Stop use and ask a doctor if

 pain gets worse or lasts more than 10 days

 fever gets worse or lasts more than 3 days

 new symptoms occur

 redness or swelling is present.

These could be signs of a serious condition.

PREGNANCY OR BREAST FEEDING

If pregnant or breast-feeding, ask a health professional before use.

Keep out of reach of children.

OVERDOSAGE

Overdose warning: In case of overdose, get medical help or contact a Poison Control Center right away (1-800-222-1222). Quick medical attention is critical for adults as well as for children even if you do not notice any signs or symptoms.

Directions

 do not take more than directed (see overdose warning).

adults and children 12 years of age and over |  take 2 caplets every 6 hours while symptoms last  do not take more than 6 caplets in 24 hours, unless directed by a doctor  do not take for more than 10 days unless directed by a doctor
children under 12 years of age |  ask a doctor

Other information

 Store in a dry place at 15° – 30°C (59° – 86°F)

INACTIVE INGREDIENT

corn starch, hypromellose, mineral oil, polyethylene glycol, povidone, sodium lauryl sulfate, sodium starch glycolate, stearic acid, talc, titanium dioxide

Questions or comments?

Call 1-800-231-4670

Distributed by: CVS Pharmacy, Inc.
One CVS Drive, Woonsocket, RI 02895
© 2021 CVS/pharmacy

*This product is not manufactured or distributed by McNeil Consumer Healthcare, owner of the registered trademark Tylenol®.

DO NOT USE IF PRINTED SEAL UNDER CAP IS BROKEN OR MISSING

PACKAGE LABEL

CVS Health

Compare to the active ingredient in Extra Strength Tylenol®*

Extra Strength

Acetaminophen

Caplets 500 mg

Pain reliever; Fever reducer

1000 Caplets